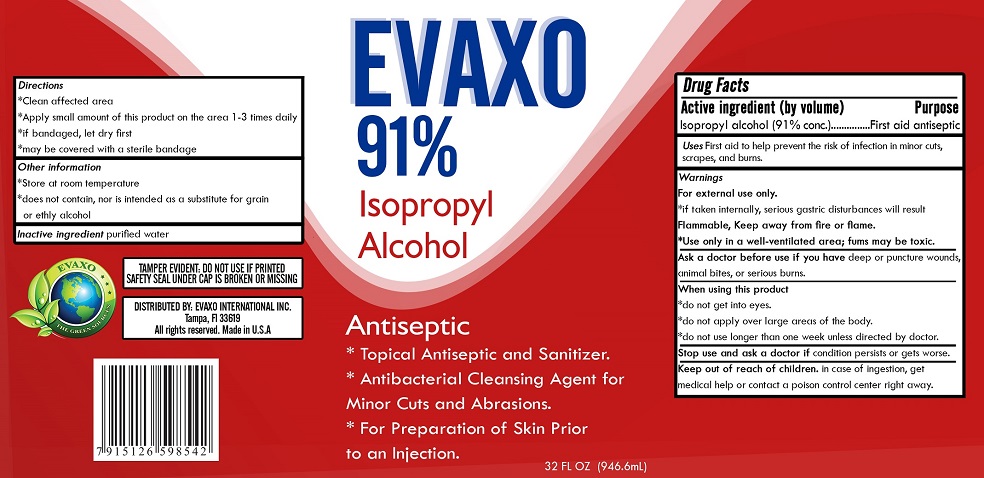 DRUG LABEL: EVAXO 91% Isopropyl Alcohol
NDC: 78376-241 | Form: LIQUID
Manufacturer: Evaxo International Inc
Category: otc | Type: HUMAN OTC DRUG LABEL
Date: 20200604

ACTIVE INGREDIENTS: ISOPROPYL ALCOHOL 91 mL/100 mL
INACTIVE INGREDIENTS: WATER

EVAXO 91% Isopropyl Alcohol

Active ingredient (by volume)

Isopropyl alcohol (91% conc.)

Purpose

First aid antiseptic

INDICATIONS AND USAGE

Uses First aid to help prevent the risk of infection in minor cuts, scrapes, and burns.

Warnings

For external use only.

*if taken internally, serious gastric disturbances will result

Flammable, Keep away from fire or flame.

*Use only in a well-ventilated area; fumes may be toxic.

Ask a doctor before use if you have deep or puncture wounds, animal bites, or serious burns.

When using this product

*do not get into eyes.

*do not apply over large areas of the body.

*do not use longer than one week unless directed by doctor.

Stop use and ask a doctor if condition persists or gets worse.

Keep out of reach of children. in case of ingestion, get medical help or contact a poison control center right away.

Directions

*Clean affected area

*Apply small amount of this product on the area 1-3 times daily

*if bandaged, let dry first

*may be covered with a sterile bandage

Other information

*Store at room temperature

*does not contain, nor is intended as a substitute for grain or ethyl alcohol

Inactive ingredient purified water

Antiseptic

* Topical Antiseptic and Sanitizer.

* Antibacterial Cleansing Agent for Minor Cuts and Abrasions.

* For Preparation of Skin Prior to an Injection.

THE GREEN SOURCES

TAMPER EVIDENT: DO NOT USE IF PRINTED SAFETY SEAL UNDER CAP IS BROKEN OR MISSING

DISTRIBUTED BY: EVAXO INTERNATIONAL INC.

Tampa, FI 33619

All rights reserved. Made in U.S.A